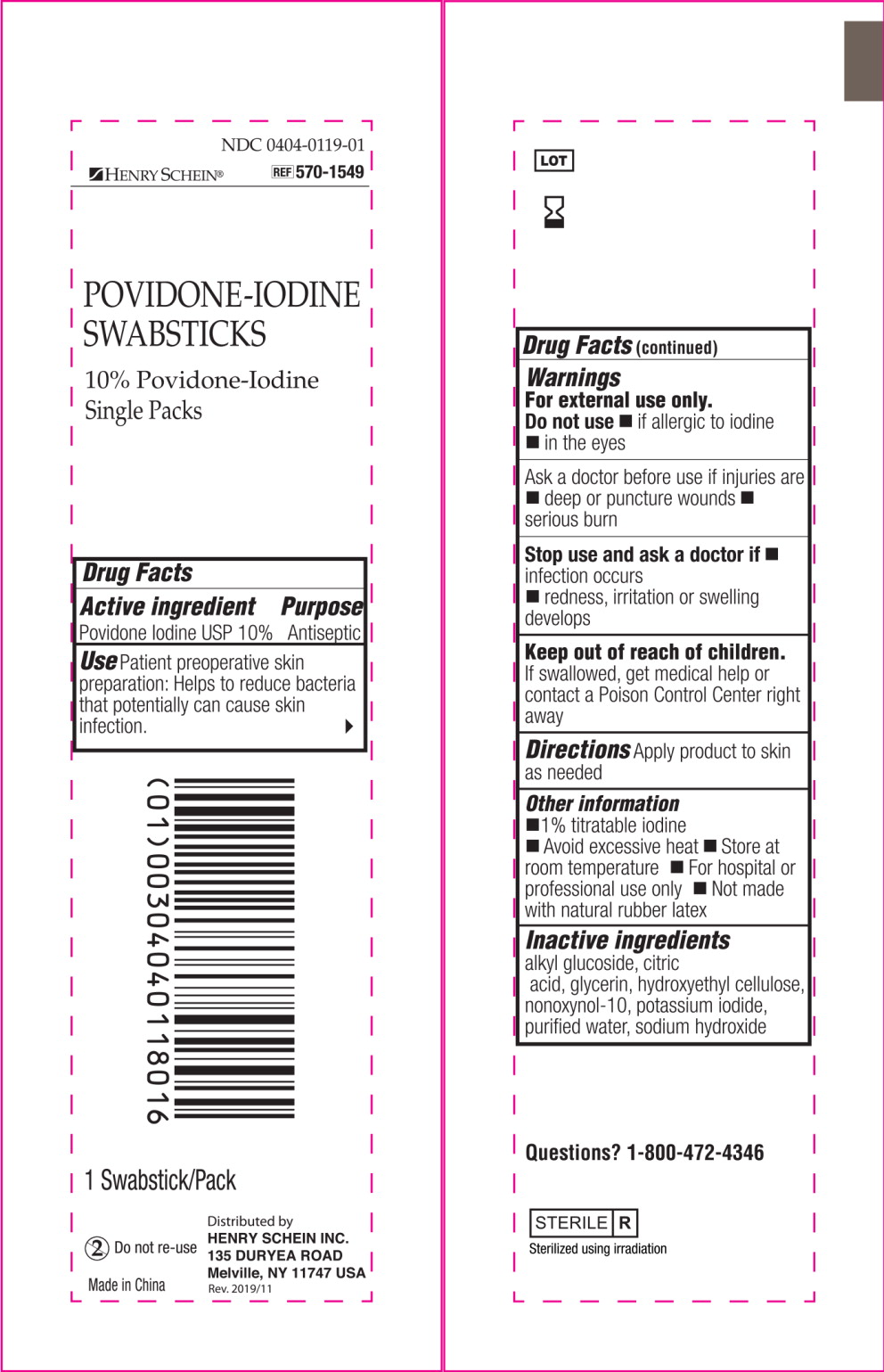 DRUG LABEL: Henry Schein Povidone-Iodine Swabsticks
NDC: 0404-0119 | Form: SWAB
Manufacturer: Henry Schein, Inc.
Category: otc | Type: HUMAN OTC DRUG LABEL
Date: 20231013

ACTIVE INGREDIENTS: POVIDONE-IODINE 1 g/100 mL
INACTIVE INGREDIENTS: GLYCERIN; HYDROXYETHYL CELLULOSE (2000 MPA.S AT 1%); NONOXYNOL-10; ANHYDROUS CITRIC ACID; SODIUM HYDROXIDE; WATER; POTASSIUM IODIDE

Drug Facts

Active ingredient

Povidone Iodine USP 10%

Purpose

Antiseptic

Use

Patient preoperative skin preparation: Helps to reduce bacteria that potentially can cause skin infection.

Warnings

For external use only.

Do not use

- if allergic to iodine
- in the eyes

Ask a doctor before use if injuries are

- deep or puncture wounds
- serious burn

Stop use and ask a doctor if

- infection occurs
- redness, irritation or swelling develops

Keep out of reach of children.

If swallowed, get medical help or contact a Poison Control Center right away

Directions

Apply product to skin as needed

Other information

- 1 % titratable iodine
- Avoid excessive heat
- Store at room temperature
- For hospital or professional use only
- Not made with natural rubber latex

Inactive ingredients

alkyl glucoside, citric acid, glycerin, hydroxyethyl cellulose, nonoxynol-10, potassium iodide, purified water, sodium hydroxide

Questions?

1-800-472-4346

Principal Display Panel - 2.3 mL Item Label

NDC 0404-0119-01

HENRY SCHEIN®

REF 570-1549

POVIDONE-IODINE
SWABSTICKS

10% Povidone-Iodine
Single Packs

1 Swabstick/Pack

Do not re-use